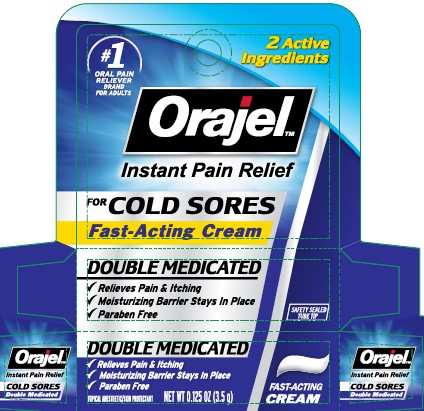 DRUG LABEL: Orajel for Cold Sores Double Medicated, Cream
NDC: 10237-797 | Form: CREAM
Manufacturer: Church & Dwight Co., Inc.
Category: otc | Type: HUMAN OTC DRUG LABEL
Date: 20251205

ACTIVE INGREDIENTS: BENZOCAINE 200 mg/1 g; PETROLATUM 736.4 mg/1 g
INACTIVE INGREDIENTS: CHOLECALCIFEROL; METHYLPARABEN; MINERAL OIL; POLYETHYLENE GLYCOL, UNSPECIFIED; PRUNELLA VULGARIS FLOWERING TOP; VITAMIN A PALMITATE; .ALPHA.-TOCOPHEROL; .ALPHA.-TOCOPHEROL ACETATE, D-; WATER; CORN OIL

Orajel for Cold Sores Double Medicated, Cream

ACTIVE INGREDIENT

Benzocaine 20%

White petrolatum 73.64%

Questions or comments?call us at 1-800-952-5080M-F 9am-5pm or visit our website at www.orajel.com

PURPOSE

Topical anesthetic

Skin protectant

INDICATIONS AND USAGE

Usetemporarily relieves pain, itching and dryness; softens crusts (scabs) associated with • cold sores • fever blisters

Warnings

For external use only

Methemoglobinemia warning:Use of this product may cause methemoglobinemia, a serious condition that must be treated promptly because it reduces the amount of oxygen carried in blood. This can occur even if you have used this product before. Stop use and seek immediate medical attention if you or a child in your care develops: • pale, gray, or blue colored skin (cyanosis) • headache • rapid heart rate • shortness of breath • dizziness or lightheadedness • fatigue or lack of energy

Allergy alert:do not use this product if you have a history of allergy to local anesthetics such as procaine, butacaine, benzocaine or other "caine" anesthetics

Do not use

- more than directed
- for more than 7 days unless directed by a physician or healthcare provider
- for teething
- in children under 2 years of age

Keep out of reach of children.

In case of overdose, get medical help or contact a Poison Control Center right away.

Directions

- cut open tube of tip on score mark
- Do not use if tip is cut prior to opening

Adults and Children 2 years of age and older: Apply to affected area not more than 3 to 4 times daily

Children betweem 2 and 12 years of age: Ask a doctor before use. Should be supervised in the use of this product

Children under 2 years of age: Do not use

INACTIVE INGREDIENT

Inactive ingredientscholecalciferol, mineral oil, phenoxyethanol (and) hydroxyacetophenone (and) caprylyl glycol (and) water, propylene glycol, prunella vulgaris leaf extract, retinyl palmitate (vitamin A palmitate), tocopherol, tocopherol acetate (vitamin E acetate), zea mays (corn) oil

PACKAGE LABEL

#1

ORAL PAIN

RELIVER

BRAND

FOR ADULTS

2 Active

Ingredients

Orajel

Instant Pain Relief

FOR COLD SORES

Fast-Acting Cream

DOUBLE MEDICATED

Relieves Pain & Itching

Moisturizing Barrier Stays in Place

Paraben Free

TOPICAL ANESTHETIC/SKIN PROTECTANT

NET WT 0.125 OZ (3.5 g)